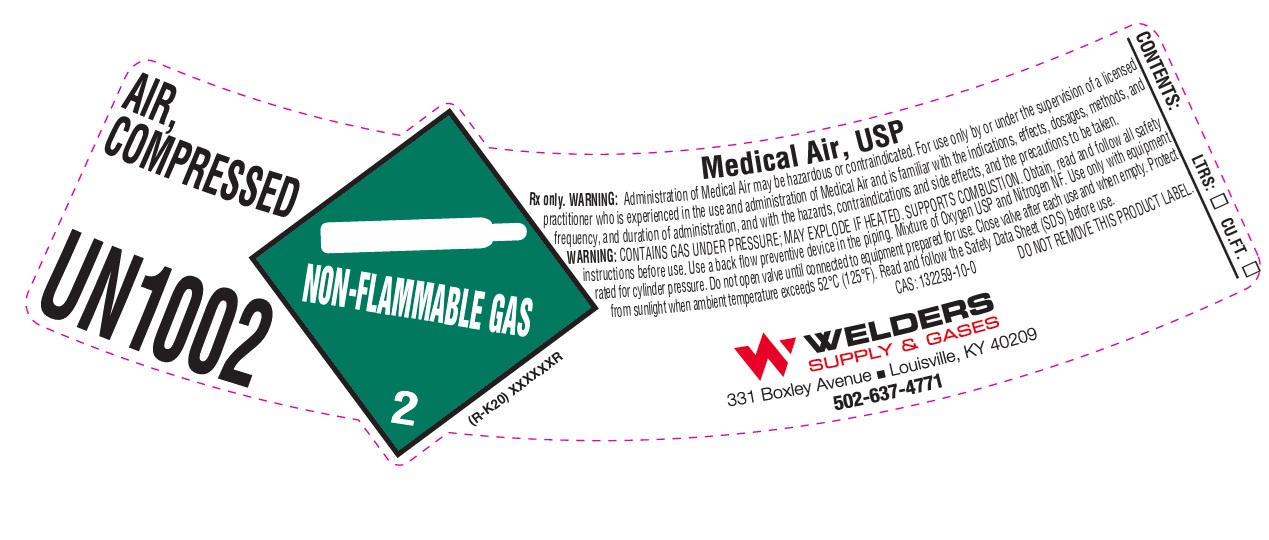 DRUG LABEL: RECONSTITUTED AIR
NDC: 84078-004 | Form: GAS
Manufacturer: WELDERS SUPPLY COMPANY OF LOUISVILLE, INC.
Category: prescription | Type: HUMAN PRESCRIPTION DRUG LABEL
Date: 20260128

ACTIVE INGREDIENTS: OXYGEN 210 mL/1 L
INACTIVE INGREDIENTS: NITROGEN 790 mL/1 L

RECONSTITUTED AIR

PACKAGE LABEL

AIR, COMPRESSED

UN1002

Medical Air, USP

Rx only. WARNING: Administration of Medical Air may be hazardous or contraindicated. For use only by or under the supervision of a licensed practitioner who is experienced in the use and administration of Medical Air and is familiar with the indications, effects, dosages, methods, and frequency, and duration of administration, and with the hazards, contraindications and side effects, and the precautions to be taken.

WARNING: CONTAINS GAS UNDER PRESSURE; MAY EXPLODE IF HEATED. SUPPORTS COMBUSTION. Obtain, read and follow all safety instructions before use. Use a back flow preventive device in the piping. Mixture of Oxygen USP and Nitrogen NF. Use only with equipment rated for cylinder pressure. Do not open valve until connected to equipment prepared for use. Close valve after each use and when empty. Protect from sunlight when ambient temperature exceeds 52 C (125 F). Read and follow the Safety Data Sheet (SDS) before use.

CAS: 132259-10-0 DO NOT REMOVE THIS PRODUCT LABEL.

WELDERS SUPPLY & GASES

331 Boxley Avenue Louisville, KY 40209

502-637-4771

CONTENTS: LTRS: CU.FT.